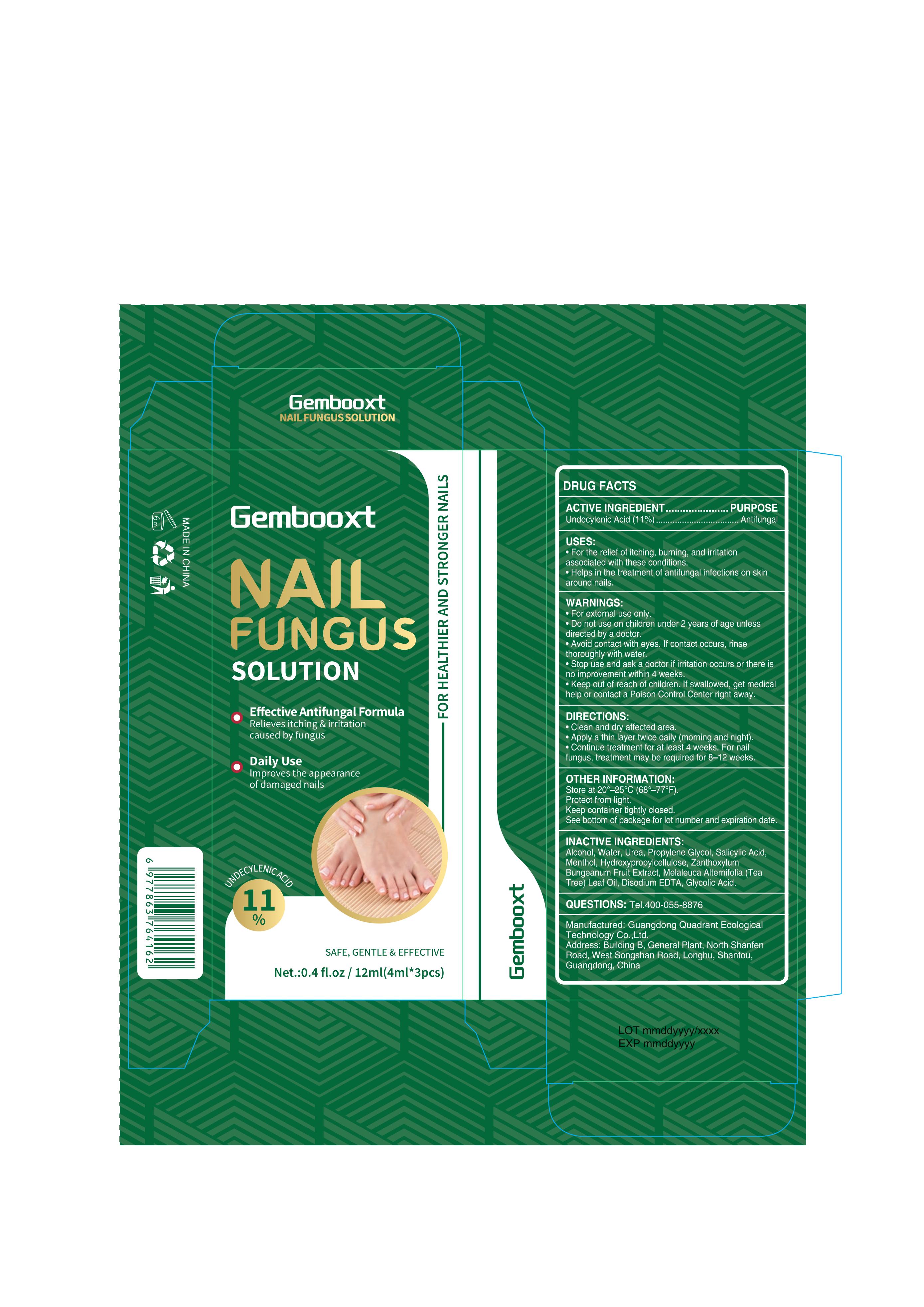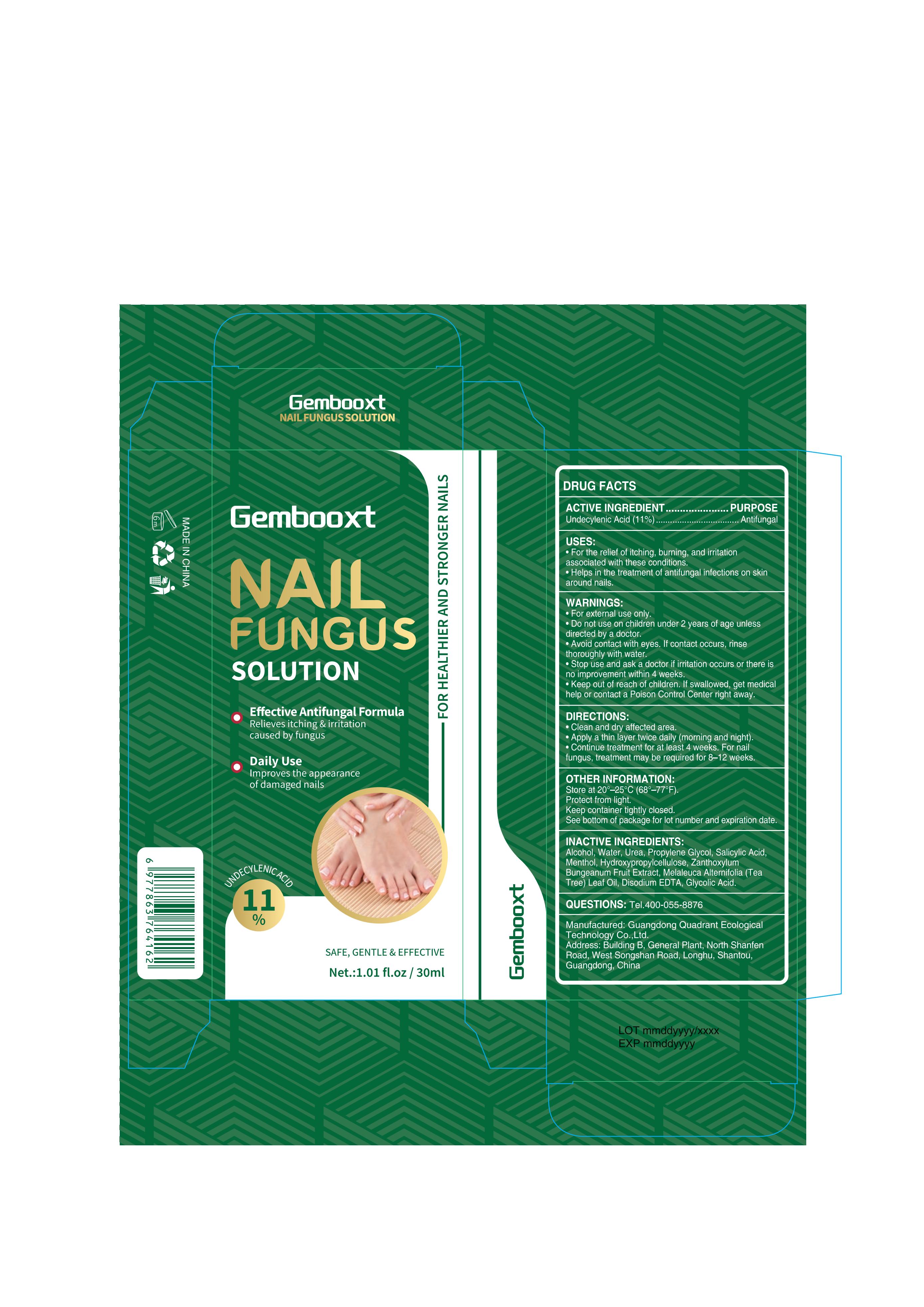 DRUG LABEL: Gembooxt Nail Fungus Solution
NDC: 76986-016 | Form: LIQUID
Manufacturer: Guangdong Quadrant Ecological Technology Co., Ltd.
Category: otc | Type: HUMAN OTC DRUG LABEL
Date: 20251202

ACTIVE INGREDIENTS: UNDECYLENIC ACID 11 g/100 mL
INACTIVE INGREDIENTS: MELALEUCA ALTERNIFOLIA (TEA TREE) LEAF OIL; ZANTHOXYLUM BUNGEANUM FRUIT; SALICYLIC ACID; ALCOHOL; WATER; PROPYLENE GLYCOL; GLYCOLIC ACID; UREA; MENTHOL; HYDROXYPROPYLCELLULOSE; EDETATE DISODIUM

76986-016

Active Ingredient

Undecylenic Acid (11%)

Purpose

Antifungal

Use

• For the relief of itching, burning, and irritation associated with these conditions.
• Helps in the treatment of antifungal infections on skin around nails.

Warnings

• For external use only.

• Do not use on children under 2 years of age unless directed by a doctor.

When Using

• Avoid contact with eyes. If contact occurs, rinse thoroughly with water.

Stop Use

• Stop use and ask a doctor if irritation occurs or there is no improvement within 4 weeks.

Ask Doctor

• Stop use and ask a doctor if irritation occurs or there is no improvement within 4 weeks.

• Keep out of reach of children. If swallowed, get medical help or contact a Poison Control Center right away.

Directions

• Clean and dry affected area.
• Apply a thin layer twice daily (morning and night).
• Continue treatment for at least 4 weeks. For nail fungus, treatment may be required for 8–12 weeks.

Other information

•Store at 20°-25C(68°-77°F).
•Protect from light.
•Keep container tightly closed.
•See bottom of package for lot number and expiration date.

Inactive ingredients

Alcohol，Water，Urea，Propylene Glycol，Salicylic Acid，Menthol ，Hydroxypropylcellulose ，Zanthoxylum Bungeanum Fruit Extract，Melaleuca Alternifolia (Tea Tree) Leaf Oil，Disodium EDTA，Glycolic Acid

Questions

Tel.400-055-8876

Manufacturerd: Guangdong Quadrant Ecological Technology Co.,Ltd.
Address: Building B, General Plant, North Shanfen Road, West Songshan Road,Longhu,Shantou,Guangdong,China